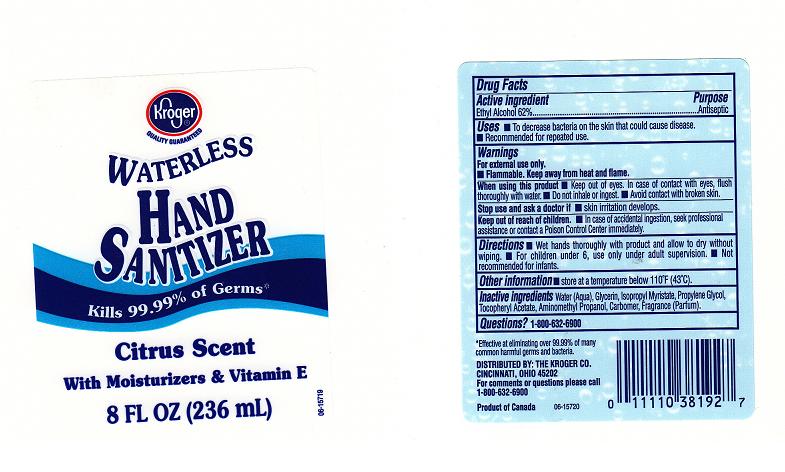 DRUG LABEL: WATERLESS HAND SANITIZER
NDC: 59450-231 | Form: GEL
Manufacturer: THE KROGER COMPANY
Category: otc | Type: HUMAN OTC DRUG LABEL
Date: 20110610

ACTIVE INGREDIENTS: ALCOHOL 62 mL/100 mL
INACTIVE INGREDIENTS: WATER; GLYCERIN; ISOPROPYL MYRISTATE; PROPYLENE GLYCOL; .ALPHA.-TOCOPHEROL ACETATE, DL-; AMINOMETHYLPROPANOL; CARBOMER 1342

DRUG FACTS

ACTIVE INGREDIENT

ETHYL ALCOHOL 62%

PURPOSE

ANTISEPTIC

USES

TO DECREASE BACTERIA ON THE SKIN

WARNINGS

FOR EXTERNAL USE ONLY, FLAMMABLE, KEEP AWAY FROM HEAT AND FLAME.

WHEN USING THIS PRODUCT

KEEP OUT OF EYES. IN CASE OF CONTACT WITH EYES, FLUSH THOROUGHLY WITH WATER. DO NOT INHALE OR INGEST. AVOID CONTACT WITH BROKEN SKIN.

STOP USE AND ASK A DOCTOR

IF SKIN IRRITATION DEVELOPS

KEEP OUT OF REACH OF CHILDREN

IN CASE OF ACCIDENTAL INGESTION, SEEK PROFESSIONAL ASSISTANCE OR CONTACT A POISON CONTROL CENTER IMMEDIATELY.

DIRECTIONS

WET HANDS THOROUGHLY WITH PRODUCT AND ALLOW TO DRY WITHOUT WIPING. FOR CHILDREN UNDER SIX, USE ONLY UNDER ADULT SUPERVISION. NOT RECOMMENDED FOR INFANTS.

QUESTIONS

1-800-632-6900

OTHER INFORMATION

STORE AT ROOM TEMPERATURE

INACTIVE INGREDIENTS

WATER, GLYCERIN, ISOPROPYL MYRISTATE, PROPYLENE GLYCOL, TOCOPHERYL ACETATE, AMINOMETHYL PROPANOL, CARBOMER, FRAGRANCE